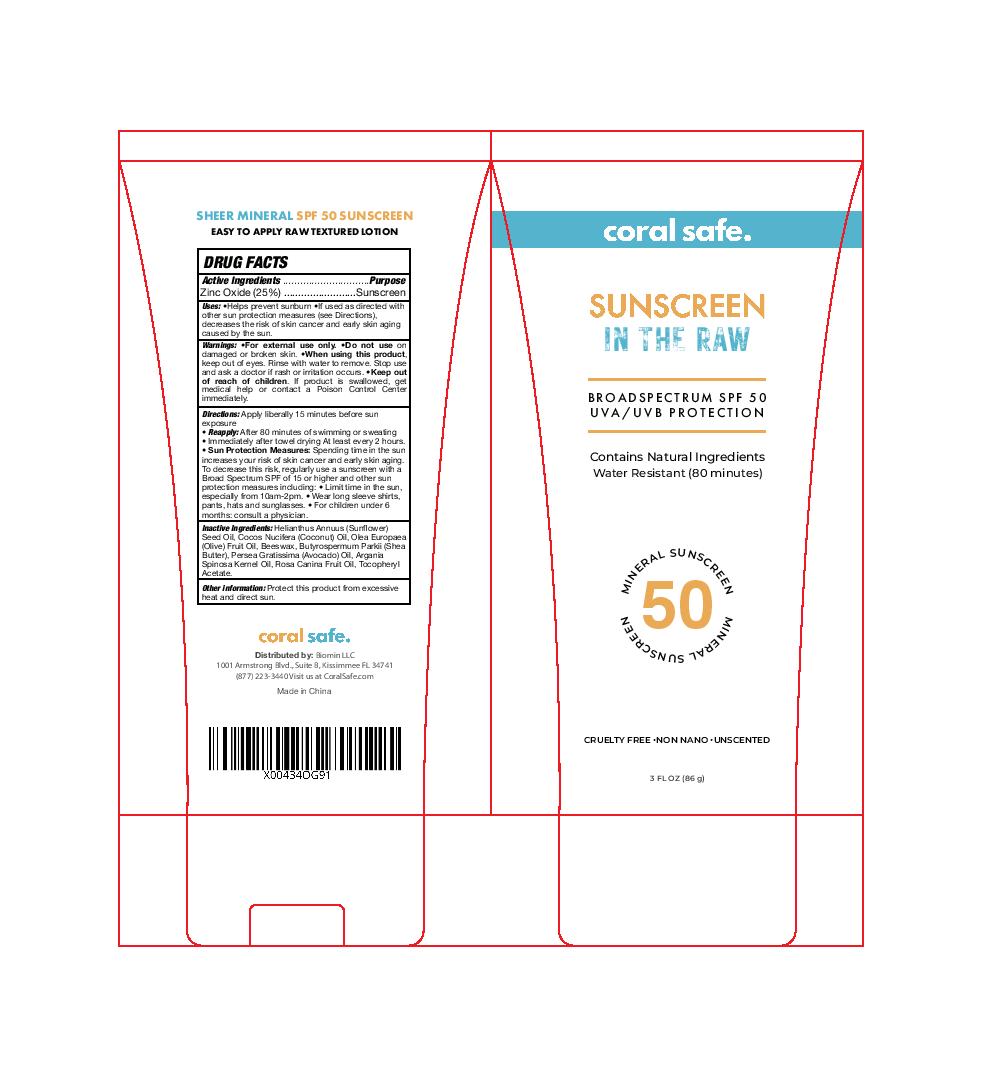 DRUG LABEL: Sunscreen In The Raw
NDC: 82177-003 | Form: LOTION
Manufacturer: Biomin LLC
Category: otc | Type: HUMAN OTC DRUG LABEL
Date: 20240220

ACTIVE INGREDIENTS: ZINC OXIDE 0.25 g/100 g
INACTIVE INGREDIENTS: ALPHA-TOCOPHEROL ACETATE; SHEA BUTTER; COCONUT OIL; SUNFLOWER SEED OIL GLYCERETH-8 ESTERS; OLIVE OIL; PEG-8 BEESWAX; ROSA CANINA FRUIT OIL; ARGANIA SPINOSA SEED; AVOCADO OIL

ACTIVE INGREDIENT

Zinc Oxide (25%)

PURPOSE

Sunscreen

INDICATIONS AND USAGE

Uses: •Helps prevent sunburn • If used as directed with
other sun protection measures (see Directions),
decreases the risk of skin cancer and early skin aging
caused by the sun

WARNINGS

Warnings: •For external use only. •Do not use on
damaged or broken skin. •When using this product, keep out of eyes. Rinse with water to remove. Stop use and ask a doctor if rash or irritation occurs. •Keep out of reach of children. If product is swallowed, get medical help or contact a Poison Control Center immediately.

DOSAGE AND ADMINISTRATION

Directions: Apply liberally 15 minutes before sun
exposure
• Reapply: After 80 minutes of swimming or sweating
• Immediately after towel drying At least every 2 hours.
• Sun Protection Measures: Spending time in the sun increases your risk of skin cancer and early skin aging. To decrease this risk, regularly use a sunscreen with a Broad Spectrum SPF of 15 or higher and other sun protection measures including:
• Limit time in the sun, especially from 10am-2pm. • Wear long sleeve shirts, pants, hats and sunglasses.
• For children under 6 months: consult a physician.

INACTIVE INGREDIENT

Inactive Ingredients: Helianthus Annuus (Sunflower) Seed Oil, Cocos Nucifera (Coconut) Oil, Olea Europaea (Olive) Fruit Oil, Beeswax, Butyrospermum Parkii (Shea Butter), Persea Gratissima (Avocado) Oil, Argania Spinosa Kernel Oil, Rosa Canina Fruit Oil, Tocopheryl Acetate.

Other information: Protect this product from excessive heat and direct sun.

•Keep out of reach of children. If product is swallowed, get medical help or contact a Poison Control Center immediately.